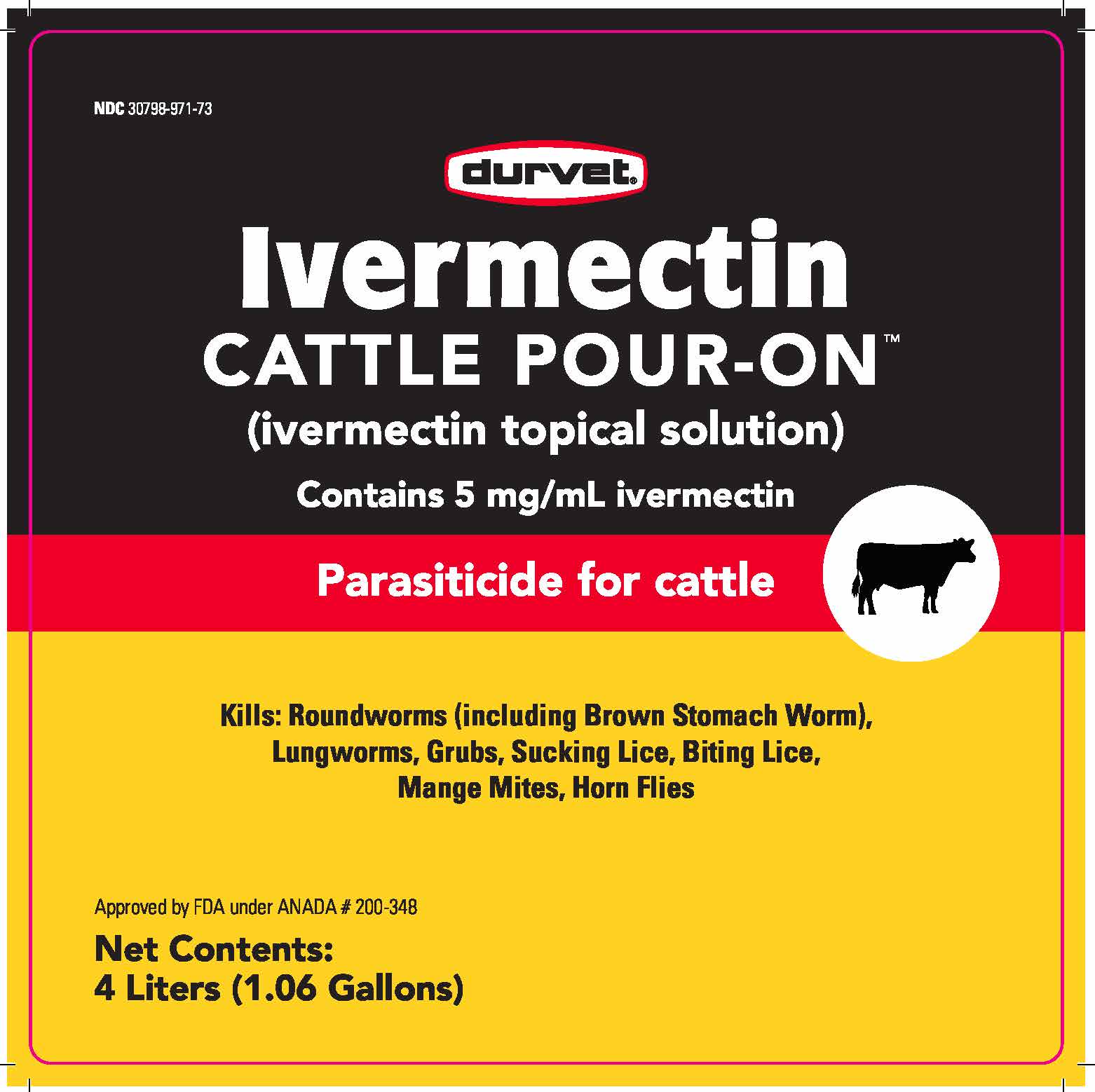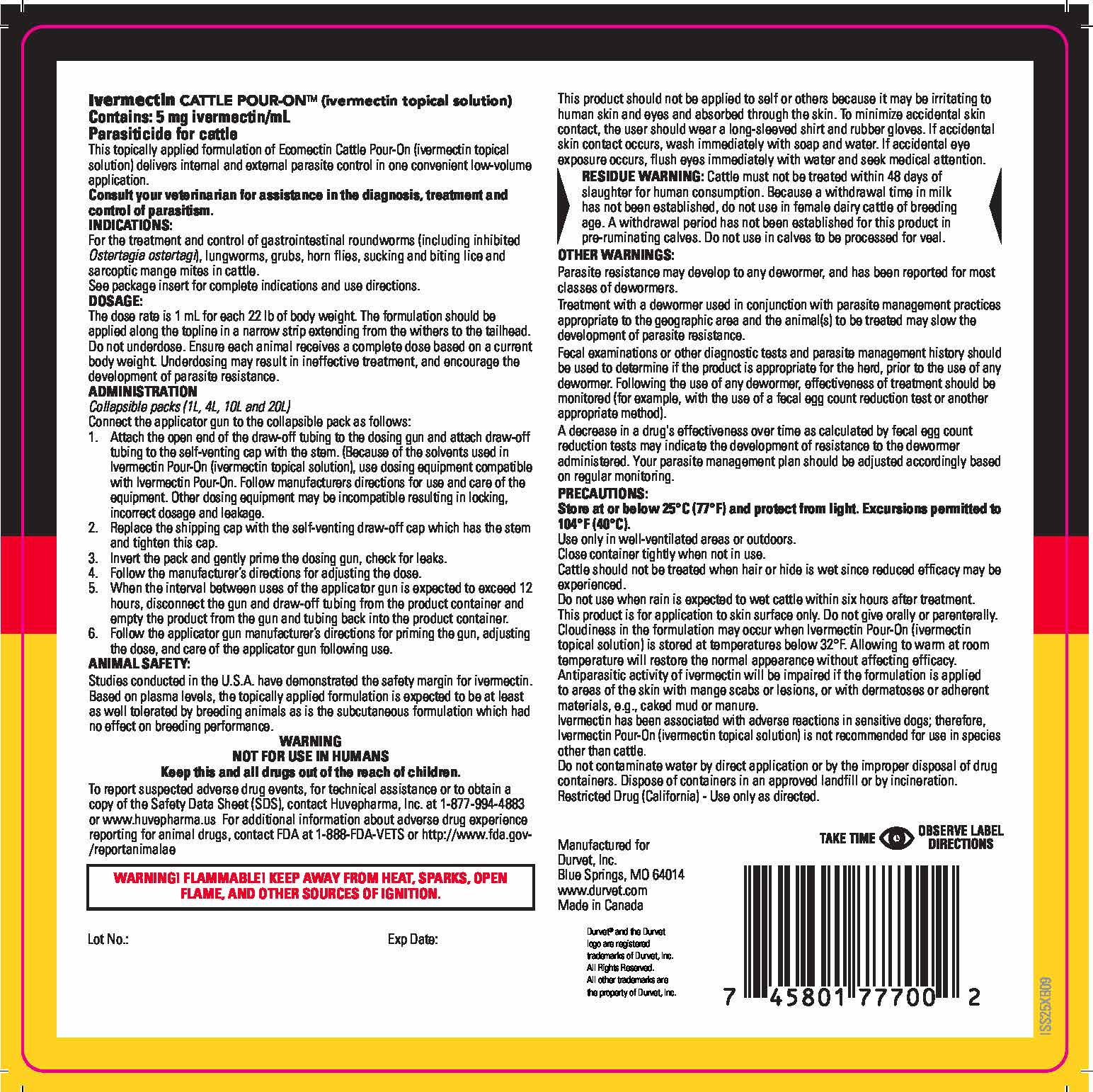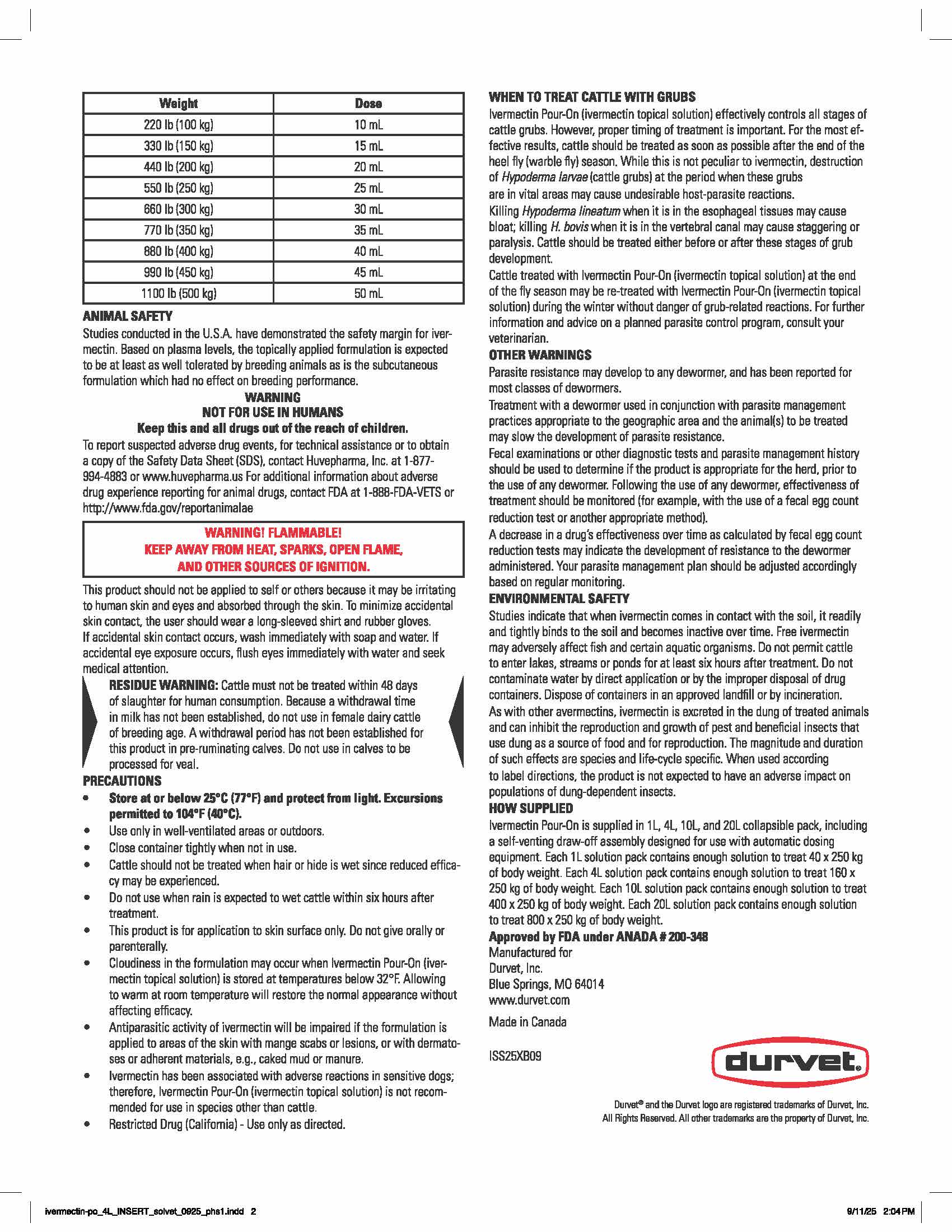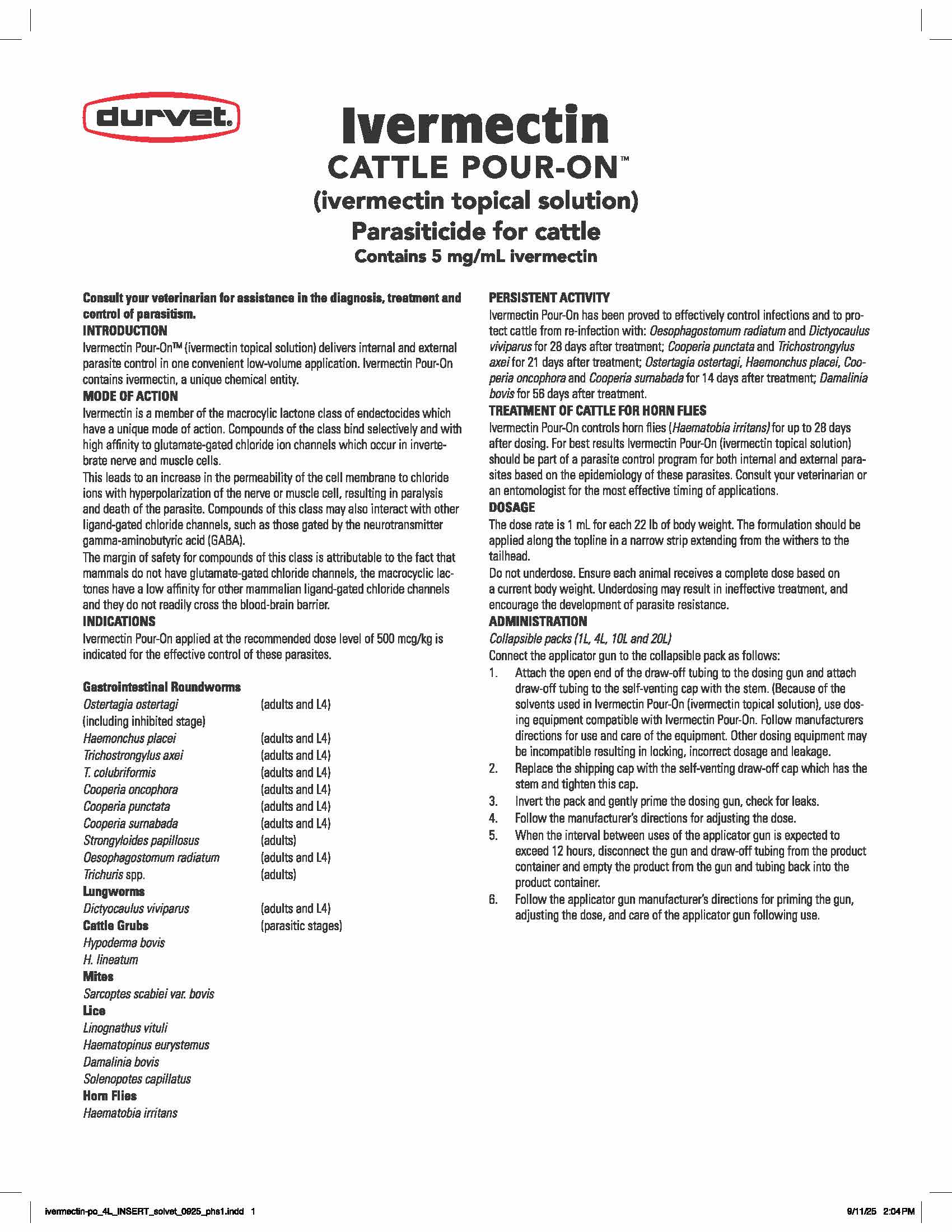 DRUG LABEL: Ivermectin Cattle Pour-On
NDC: 30798-971 | Form: SOLUTION
Manufacturer: Durvet, Inc.
Category: animal | Type: OTC ANIMAL DRUG LABEL
Date: 20250609

ACTIVE INGREDIENTS: ivermectin 5 mg/1 mL
INACTIVE INGREDIENTS: CETEARYL ETHYLHEXANOATE

Ivermectin
CATTLE POUR-ON
(ivermectin topical solution)
Parasiticide for cattle
Contains 5 mg/mL ivermectin

Consult your veterinarian for assistance in the diagnosis, treatment and control of parasitism.

INTRODUCTION
Ivermectin Pour-On™ (ivermectin topical solution) delivers internal and external parasite control in one convenient low-volume application.
Ivermectin Pour-On contains ivermectin, a unique chemical entity.

MODE OF ACTION
Ivermectin is a member of the macrocylic lactone class of endectocides which have a unique mode of action. Compounds of the class
bind selectively and with high affinity to glutamate-gated chloride ion channels which occur in invertebrate nerve and muscle cells.

This leads to an increase in the permeability of the cell membrane to chloride ions with hyperpolarization of the nerve or muscle
cell, resulting in paralysis and death of the parasite. Compounds of this class may also interact with other ligand-gated chloride
channels, such as those gated by the neurotransmitter gamma-aminobutyric acid (GABA).

The margin of safety for compounds of this class is attributable to the fact that mammals do not have glutamate-gated chloride
channels, the macrocyclic lactones have a low affinity for other mammalian ligand-gated chloride channels and they do not readily
cross the blood-brain barrier.

INDICATIONS
Ivermectin Pour-On applied at the recommended dose level of 500 mcg/kg is indicated for the effective control of these parasites.

Gastrointestinal Roundworms
Ostertagia ostertagi; (including inhibited stage) | (adults and L4)
Haemonchus placei | (adults and L4)
Trichostrongylus axei | (adults and L4)
T. colubriformis | (adults and L4)
Cooperia oncophora | (adults and L4)
Cooperia punctata | (adults and L4)
Cooperia surnabada | (adults and L4)
Strongyloides papillosus | (adults)
Oesophagostomum radiatum | (adults and L4)
Trichuris spp. | (adults)
Lungworms
Dictyocaulus viviparus | (adults and L4)
Cattle Grubs | (parasitic stages)
Hypoderma bovis
H. lineatum
Mites
Sarcoptes scabiei var. bovis
Lice
Linognathus vituli
Haematopinus eurystemus
Damalinia bovis
Solenopotes capillatus
Horn Flies
Haematobia irritans

PERSISTENT ACTIVITY
Ivermectin Pour-On has been proved to effectively control infections and to protect cattle from re-infection with: Oesophagostomum
radiatum and Dictyocaulus viviparus for 28 days after treatment; Cooperia punctata and Trichostrongylus axei for 21 days after treatment;
Ostertagia ostertagi, Haemonchus placei, Cooperia oncophora and Cooperia surnabada for 14 days after treatment; Damalinia bovis for 56
days after treatment.

TREATMENT OF CATTLE FOR HORN FLIES
Ivermectin Pour-On controls controls horn flies (Haematobia irritans) for up to 28 days after dosing. For best results Ivermectin Pour-On
(ivermectin topical solution) should be part of a parasite control program for both internal and external parasites based on the epidemiology
of these parasites. Consult your veterinarian or an entomologist for the most effective timing of applications.

DOSAGE
The dose rate is 1 mL for each 22 lb of body weight. The formulation should be applied along the topline in a narrow strip extending from
the withers to the tailhead.
Do not underdose. Ensure each animal receives a complete dose based on a current body weight. Underdosing may result in ineffective treatment,
and encourage the development of parasite resistance.

ADMINISTRATION
Collapsible packs (1L, 4L, 10L and 20L)

Connect the applicator gun to the collapsible pack as follows:
1. Attach the open end of the draw-off tubing to the dosing gun and attach draw-off tubing to the self-venting cap with the stem.
(Because of the solvents used in Ivermectin Pour-On (ivermectin topical solution), use dosing equipment compatible with Ivermectin
Pour-On. Follow manufacturers directions for use and care of the equipment. Other dosing equipment may be incompatible resulting
in locking, incorrect dosage and leakage.
2. Replace the shipping cap with the self-venting draw-off cap which has the stem and tighten this cap.
3. Invert the pack and gently prime the dosing gun, check for leaks.
4. Follow the manufacturer’s directions for adjusting the dose.
5. When the interval between uses of the applicator gun is expected to exceed 12 hours, disconnect the gun and draw-off tubing from the
product container and empty the product from the gun and tubing back into the product container.
6. Follow the applicator gun manufacturer’s directions for priming the gun, adjusting the dose, and care of the applicator gun following use.

Weight | Dose
220 lb (100 kg) | 10 mL
330 lb (150 kg) | 15 mL
440 lb (200 kg) | 20 mL
550 lb (250 kg) | 25 mL
660 lb (300 kg) | 30 mL
770 lb (350 kg) | 35 mL
880 lb (400 kg) | 40 mL
990 lb (450 kg) | 45 mL
1100 lb (500 kg) | 50 mL

ANIMAL SAFETY
Studies conducted in the U.S.A. have demonstrated the safety margin for ivermectin. Based on plasma levels, the topically
applied formulation is expected to be at least as well tolerated by breeding animals as is the subcutaneous formulation which
had no effect on breeding performance.

WARNING
NOT FOR USE IN HUMANS
Keep this and all drugs out of the reach of children.
To report suspected adverse drug events, for technical assistance or to obtain a copy of the Safety Data Sheet (SDS),
contact Huvepharma, Inc. at 1-877-994-4883 or www.huvepharma.us. For additional information about adverse
drug experience reporting for animal drugs, contact FDA at 1-888-FDA-VETS or http://www.fda.gov/reportanimalae

WARNING! FLAMMABLE!
KEEP AWAY FROM HEAT, SPARKS, OPEN FLAME,
AND OTHER SOURCES OF IGNITION.

This product should not be applied to self or others because it may be irritating to human skin and eyes and absorbed through
the skin. To minimize accidental skin contact, the user should wear a long-sleeved shirt and rubber gloves. If accidental skin
contact occurs, wash immediately with soap and water. If accidental eye exposure occurs, flush eyes immediately with
water and seek medical attention.

RESIDUE WARNING

RESIDUE WARNING: Cattle must not be treated within 48 days of slaughter for human consumption. Because a
withdrawal time in milk has not been established, do not use in female dairy cattle of breeding age. A withdrawal period
has not been established for this product in pre-ruminating calves. Do not use in calves to be processed for veal.

PRECAUTIONS
• Store at or below 25°C (77°F) and protect from light.
Excursions permitted to 104°F (40°C).
• Use only in well-ventilated areas or outdoors.
• Close container tightly when not in use.
• Cattle should not be treated when hair or hide is wet since
reduced efficacy may be experienced.
• Do not use when rain is expected to wet cattle within six hours
after treatment.
• This product is for application to skin surface only. Do not give
orally or parenterally.
• Cloudiness in the formulation may occur when Ivermectin Cattle
Pour-On (ivermectin topical solution) is stored at temperatures
below 32°F. Allowing to warm at room temperature will restore
the normal appearance without affecting efficacy.
• Antiparasitic activity of ivermectin will be impaired if the
formulation is applied to areas of the skin with mange scabs or
lesions, or with dermatoses or adherent materials, e.g., caked
mud or manure.
• Ivermectin has been associated with adverse reactions in
sensitive dogs; therefore, Ivermectin Cattle Pour-On (ivermectin
topical solution) is not recommended for use in species other
than cattle.
• Restricted Drug (California) - Use only as directed.

INFORMATION FOR OWNERS/CAREGIVERS

WHEN TO TREAT CATTLE WITH GRUBS
Ivermectin Pour-On (ivermectin topical solution) effectively controls all stages of cattle grubs. However, proper timing of
treatment is important. For the most effective results, cattle should be treated as soon as possible after the end of the heel fly (warble
fly) season. While this is not peculiar to ivermectin, destruction of Hypoderma larvae (cattle grubs) at the period when these grubs
are in vital areas may cause undesirable host-parasite reactions.

Killing Hypoderma lineatum when it is in the esophageal tissues
may cause bloat; killing H. bovis when it is in the vertebral canal may cause staggering or paralysis. Cattle should be treated either
before or after these stages of grub development.

Cattle treated with Ivermectin Pour-On (ivermectin topical solution) at the end of the fly season may be re-treated with
Ivermectin Pour-On (ivermectin topical solution) during the winter without danger of grub-related reactions. For further
information and advice on a planned parasite control program, consult your veterinarian.

OTHER WARNINGS
Parasite resistance may develop to any dewormer, and has been reported for most classes of dewormers.

Treatment with a dewormer used in conjunction with parasite management practices appropriate to the geographic area and the
animal(s) to be treated may slow the development of parasite resistance.

Fecal examinations or other diagnostic tests and parasite management history should be used to determine if the product is
appropriate for the herd, prior to the use of any dewormer. Following the use of any dewormer, effectiveness of treatment
should be monitored (for example, with the use of a fecal egg count reduction test or another appropriate method).

A decrease in a drug's effectiveness over time as calculated by fecal egg count reduction tests may indicate the development of
resistance to the dewormer administered. Your parasite management plan should be adjusted accordingly based on regular monitoring.

ENVIRONMENTAL SAFETY
Studies indicate that when ivermectin comes in contact with the soil, it readily and tightly binds to the soil and becomes inactive
over time. Free ivermectin may adversely affect fish and certain aquatic organisms. Do not permit cattle to enter lakes, streams
or ponds for at least six hours after treatment. Do not contaminate water by direct application or by the improper
disposal of drug containers. Dispose of containers in an approved landfill or by incineration.

As with other avermectins, ivermectin is excreted in the dung of treated animals and can inhibit the reproduction and growth of
pest and beneficial insects that use dung as a source of food and for reproduction. The magnitude and duration of such
effects are species and life-cycle specific. When used according to label directions, the product is not expected to have an
adverse impact on populations of dung-dependent insects.

HOW SUPPLIED
Ivermectin Pour-On is supplied in 1L, 4L, 10L, and 20L
collapsible pack, including a self-venting draw-off assembly
designed for use with automatic dosing equipment. Each 1L
solution pack contains enough solution to treat 40 x 250 kg of body
weight. Each 4L solution pack contains enough solution to treat
160 x 250 kg of body weight. Each 10L solution pack contains
enough solution to treat 400 x 250 kg of body weight. Each 20L
solution pack contains enough solution to treat 800 x 250 kg of
body weight.

Approved by FDA under ANADA # 200-348
Manufactured for
Durvet, Inc.
Blue Springs, MO 64014
Made in Canada